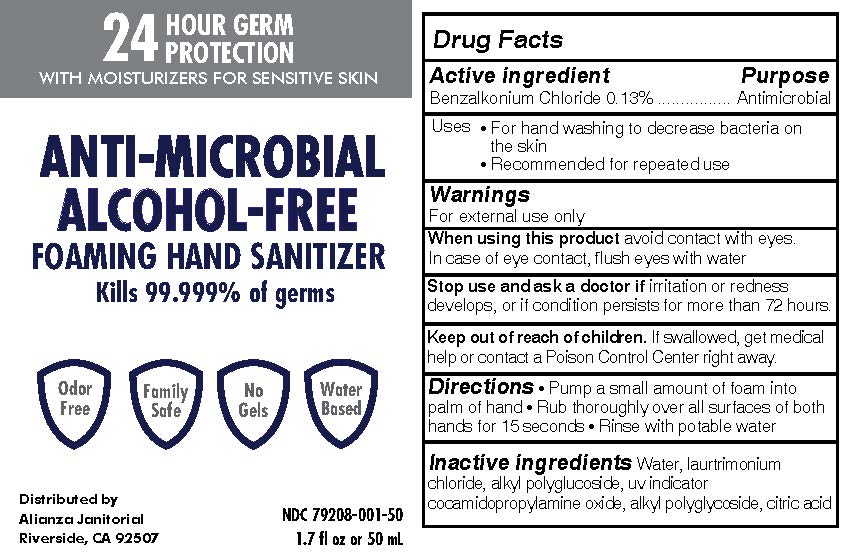 DRUG LABEL: Anti-microbial Alcohol Free Hand Sanitizer
NDC: 79208-001 | Form: LIQUID
Manufacturer: Ultra Chem Labs
Category: otc | Type: HUMAN OTC DRUG LABEL
Date: 20200804

ACTIVE INGREDIENTS: BENZALKONIUM CHLORIDE 0.13 mg/1 mg
INACTIVE INGREDIENTS: ANHYDROUS CITRIC ACID 0.2 mg/1 mg

ACTIVE INGREDIENT

Benzalkonium Chloride 0.13%

Keep out of reach of children. If swallowed, get medical help or contact a Poison Control Center right away.

Stop use and ask a doctor if irritation or redness develops, or if condition persists for more than 72 hours.

When using this product avoid contact with eyes. In case of eye contact, flush eyes with water

OTHER SAFETY INFORMATION

Directions • Pump a small amount of foam into palm of hand • Rub thoroughly over all surfaces of both hands for 15 seconds • Rinse with potable water

INACTIVE INGREDIENT

Inactive ingredients Water, laurtrimonium chloride, alkyl polyglucoside, uv indicator cocamidopropylamine oxide, alkyl polyglycoside, citric acid

Warnings
For external use only

DOSAGE AND ADMINISTRATION

Pump a small amount of foam into palm of hand • Rub thoroughly over all surfaces of both hands for 15 seconds • Rinse with potable water

INDICATIONS AND USAGE

• For hand washing to decrease bacteria on the skin
• Recommended for repeated use

PURPOSE

Antimicrobial